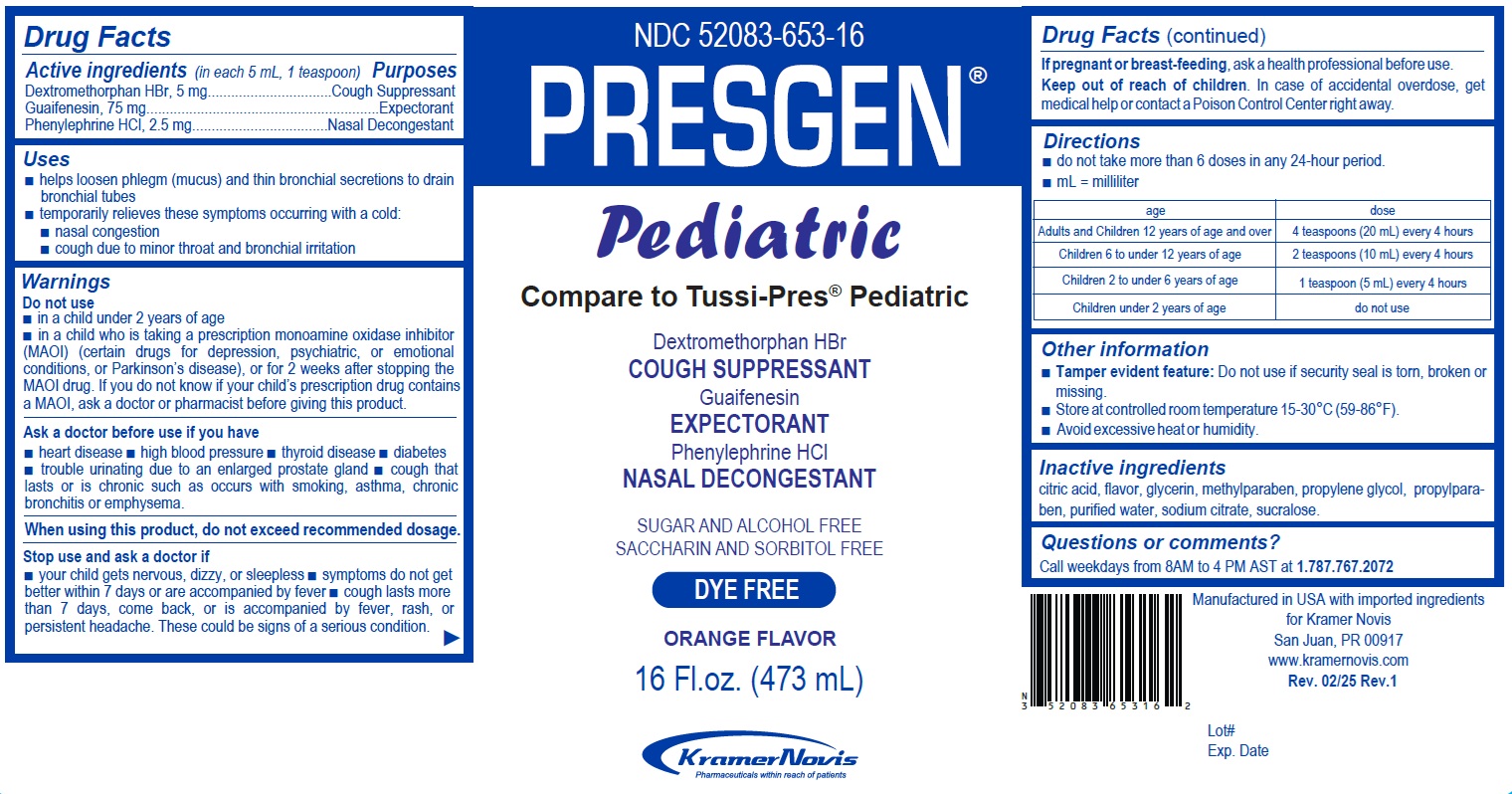 DRUG LABEL: PRESGEN PEDIATRIC
NDC: 52083-653 | Form: SYRUP
Manufacturer: KRAMER NOVIS
Category: otc | Type: HUMAN OTC DRUG LABEL
Date: 20251112

ACTIVE INGREDIENTS: DEXTROMETHORPHAN HYDROBROMIDE 5 mg/5 mL; GUAIFENESIN 75 mg/5 mL; PHENYLEPHRINE HYDROCHLORIDE 2.5 mg/5 mL
INACTIVE INGREDIENTS: CITRIC ACID MONOHYDRATE; GLYCERIN; METHYLPARABEN; PROPYLENE GLYCOL; PROPYLPARABEN; WATER; SODIUM CITRATE, UNSPECIFIED FORM; SUCRALOSE

PRESGEN PEDIATRIC

Active ingredients (in each 5 mL, 1 teaspoon)

Dextromethorphan HBr, 5 mg
Guaifenesin, 75 mg
Phenylephrine HCl, 2.5 mg

Purposes

Cough Suppressant
Expectorant
Nasal Decongestant

Uses

• helps loosen phlegm (mucus) and thin bronchial secretions to drain bronchial tubes
• temporarily relieves these symptoms occurring with a cold:
• nasal congestion
• cough due to minor throat and bronchial irritation

Warnings

Do not use
• in a child under 2 years of age
• in a child who is taking a prescription monoamine oxidase inhibitor (MAOI) (certain drugs for depression, psychiatric, or emotional conditions, or Parkinson’s disease), or for 2 weeks after stopping the MAOI drug. If you do not know if your child’s prescription drug contains a MAOI, ask a doctor or pharmacist before giving this product.

Ask a doctor before use if you have
• heart disease • high blood pressure • thyroid disease • diabetes • trouble urinating due to an enlarged prostate gland • cough that lasts or is chronic such as occurs with smoking, asthma, chronic bronchitis or emphysema.

When using this product, do not exceed recommended dosage.

Stop use and ask a doctor if
• your child gets nervous, dizzy, or sleepless • symptoms do not get better within 7 days or are accompanied by fever • cough lasts more than 7 days, come back, or is accompanied by fever, rash, or persistent headache. These could be signs of a serious condition.

If pregnant or breast-feeding, ask a health professional before use.

Keep out of reach of children. In case of accidental overdose, get medical help or contact a Poison Control Center right away.

Directions

• do not take more than 6 doses in any 24-hour period.
• mL = milliliter

age | dose
Adults and Children 12 years of age and over | 4 teaspoons (20 mL) every 4 hours
Children 6 to under 12 years of age | 2 teaspoons (10 mL) every 4 hours
Children 2 to under 6 years of age | 1 teaspoon (5 mL) every 4 hours
Children under 2 years of age | do not use

Other information

• Tamper evident feature: Do not use if security seal is torn, broken or missing.
• Store at controlled room temperature 15-30°C (59-86°F).
• Avoid excessive heat and humidity.

Inactive ingredients

citric acid, flavor, glycerin, methylparaben, propylene glycol, propylparaben, purified water, sodium citrate, sucralose.

Questions or comments?

Call weekdays from 8AM to 4 PM AST at 1.787.767.2072

Compare to Tussi-Pres® Pediatric

Dextromethorphan HBr
COUGH SUPPRESSANTGuaifenesin
EXPECTORANTPhenylephrine HCl
NASAL DECONGESTANT

SUGAR AND ALCOHOL FREE
SACCHARIN AND SORBITOL FREE
DYE FREE

ORANGE FLAVOR

KramerNovis
Pharmaceuticals within reach of patients

Manufactured in USA with imported ingredients for Kramer Novis
San Juan, PR 00917
www.kramernovis.com